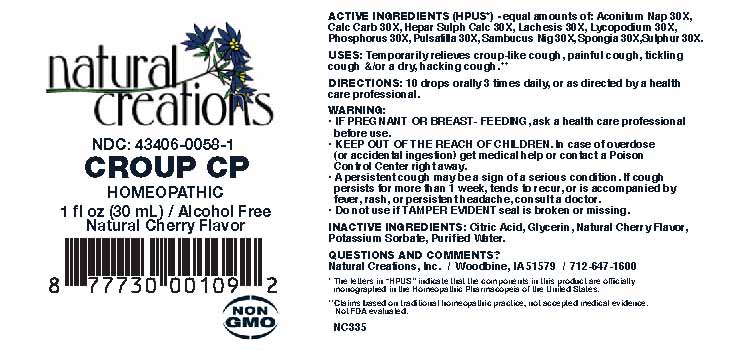 DRUG LABEL: CROUP CP
NDC: 43406-0058 | Form: LIQUID
Manufacturer: Natural Creations, Inc
Category: homeopathic | Type: HUMAN OTC DRUG LABEL
Date: 20221219

ACTIVE INGREDIENTS: ACONITUM NAPELLUS 30 [hp_X]/1 mL; OYSTER SHELL CALCIUM CARBONATE, CRUDE 30 [hp_X]/1 mL; CALCIUM SULFIDE 30 [hp_X]/1 mL; LACHESIS MUTA VENOM 30 [hp_X]/1 mL; LYCOPODIUM CLAVATUM SPORE 30 [hp_X]/1 mL; PHOSPHORUS 30 [hp_X]/1 mL; ANEMONE PULSATILLA 30 [hp_X]/1 mL; SAMBUCUS NIGRA FLOWERING TOP 30 [hp_X]/1 mL; SPONGIA OFFICINALIS SKELETON, ROASTED 30 [hp_X]/1 mL; SULFUR 30 [hp_X]/1 mL
INACTIVE INGREDIENTS: CITRIC ACID ACETATE; GLYCERIN; POTASSIUM SORBATE; WATER

CROUP CP

ACTIVE INGREDIENT

ACTIVE INGREDIENTS (HPUS*) - equal amounts of: Aconitum Nap 30X, Calc Carb 30X, Hepar Sulph Calc 30X, Lachesis 30X, Lycopodium 30X, Phosphorus 30X, Pulsatilla 30X, Sambucus Nig 30X, Spongia 30X, Sulphur 30X.

INDICATIONS AND USAGE

USES: Temporarily relieves croup-like cough, painful cough, tickling cough &/or a dry, hacking cough.**

PURPOSE

USES: Temporarily relieves croup-like cough, painful cough, tickling cough &/or a dry, hacking cough.**

DOSAGE AND ADMINISTRATION

DIRECTIONS: 10 drops orally 3 times daily, or as directed by a health care professional.

KEEP OUT OF REACH OF CHILDREN

KEEP OUT OF THE REACH OF CHILDREN. In case of overdose (or accidental ingestion) get medical help or contact a Poison Control Center right away.

WARNINGS:

- IF PREGNANT OR BREAST-FEEDING, ask a health care professional before use.
- KEEP OUT OF THE REACH OF CHILDREN. In case of overdose (or accidental ingestion) get medical help or contact a Poison Control Center right away.
- A persistant cough may be a sign of a serious condition. If cough persists for more than 1 week, tends to recur, or is accompanied by fever, rash, or persistent headache, consult a doctor.
- Do not use if TAMPER EVIDENT seal is broken or missing.

INACTIVE INGREDIENT

INACTIVE INGREDIENTS: Citric Acid, Glycerin, Natural Cherry Flavor, Potassium Sorbate, Purified Water.

QUESTIONS & COMMENTS?

Natural Creations, Inc. / Woodbine, IA 51579 / 712-647-1600

REFERENCES

*The letters "HPUS" indicate that the components in this product are officially monographed in the Homeopathic Pharmacopeia of the United States.

**Claims based on traditional homeopathic practice, not accepted medical evidence. Not FDA evaluated.

PACKAGE LABEL

NDC: 43406-0058-1

CROUP CP

HOMEOPATHIC

1 fl oz (30 mL) / Alcohol Free

Natural Cherry Flavor

877730001092